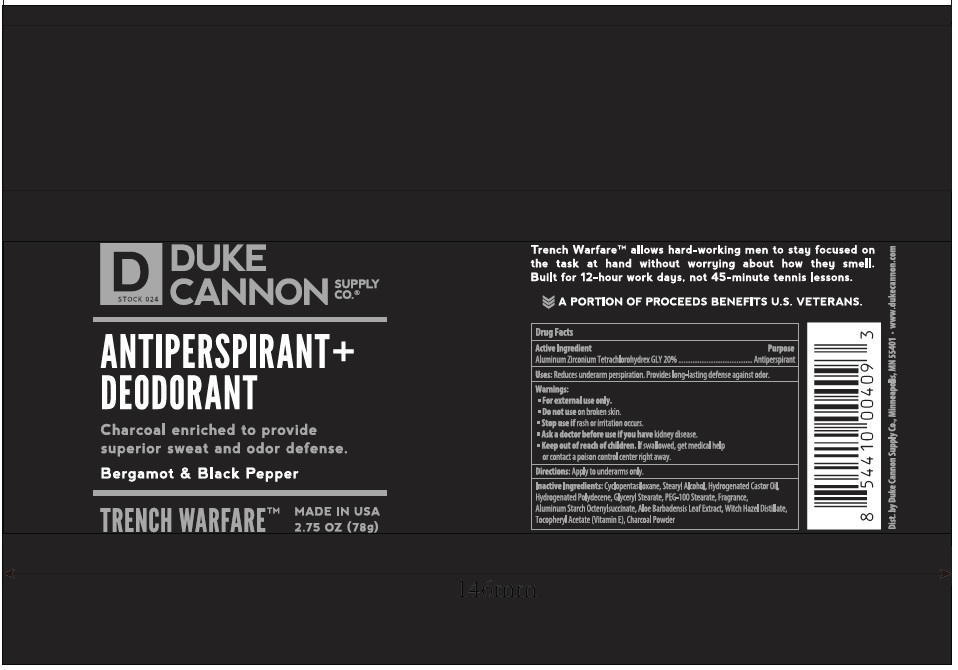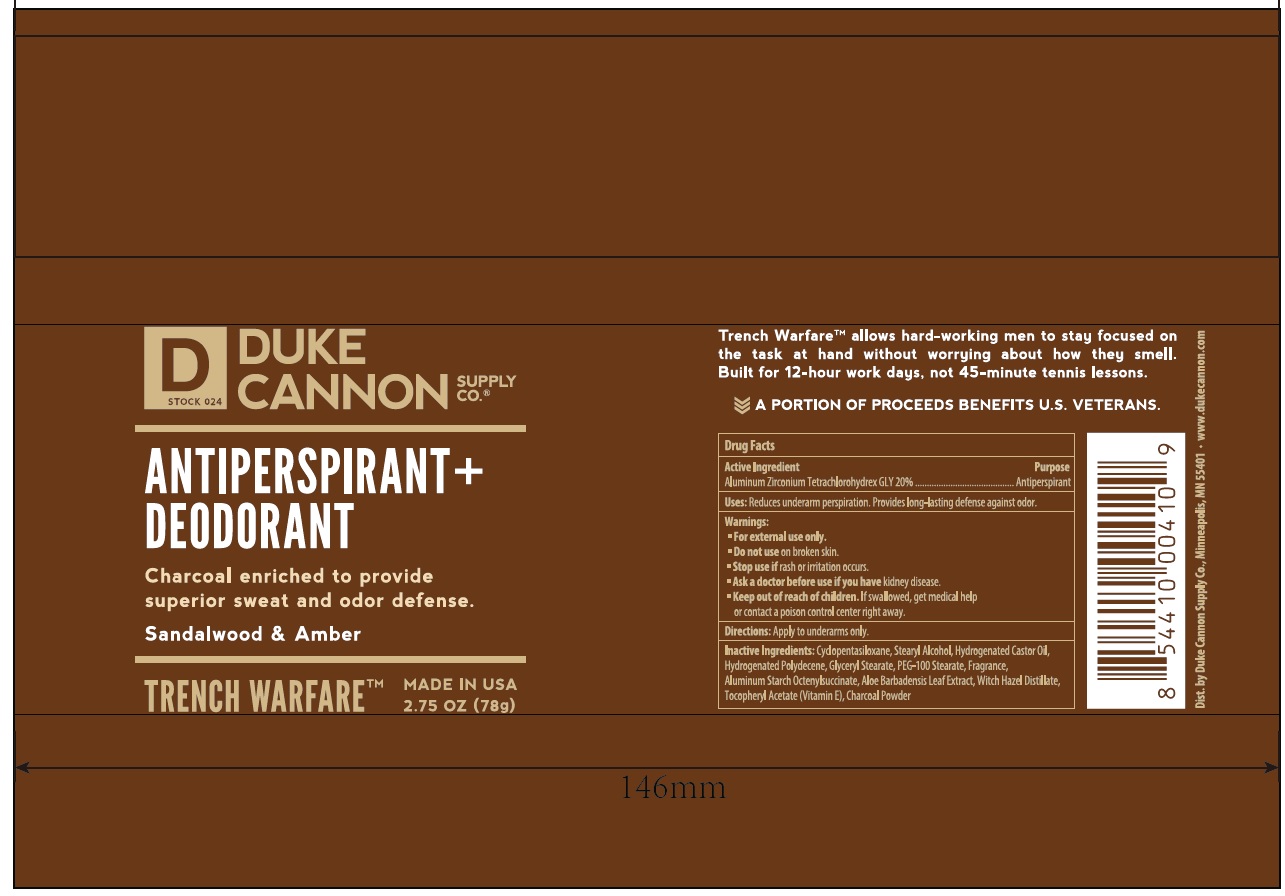 DRUG LABEL: Trench Warfare Antiperspirant and Deodorant
NDC: 71782-901 | Form: STICK
Manufacturer: DUKE CANNON SUPPLY CO.
Category: otc | Type: HUMAN OTC DRUG LABEL
Date: 20190110

ACTIVE INGREDIENTS: ALUMINUM ZIRCONIUM TETRACHLOROHYDREX GLY 20 g/100 g
INACTIVE INGREDIENTS: CYCLOMETHICONE 5; STEARYL ALCOHOL; HYDROGENATED CASTOR OIL; HYDROGENATED POLYDECENE (550 MW); GLYCERYL MONOSTEARATE; PEG-100 STEARATE; ALUMINUM STARCH OCTENYLSUCCINATE; ALOE VERA LEAF; WITCH HAZEL; .ALPHA.-TOCOPHEROL ACETATE; ACTIVATED CHARCOAL

Active ingredient

Aluminum Zirconium Tetrachlorohydrex GLY 20%

Purpose

Antiperspirant

INDICATIONS AND USAGE

Uses: Reduces underarm perspiration. Provides long-lasting defense against odor.

Warnings:

• For external use only.

• Do not use on broken skin.

• Stop use if rash or irritation occurs.

• Ask a doctor before use if you have kidney disease.

• Keep out of reach of children. If swallowed, get medical help

or contact a poison control center right away.

DOSAGE AND ADMINISTRATION

Directions: Apply to underarms only.

INACTIVE INGREDIENT

Inactive Ingredients: Cyclopentasiloxane, Stearyl Alcohol, Hydrogenated Castor Oil,

Hydrogenated Polydecene, Glyceryl Stearate, PEG-100 Stearate, Fragrance,

Aluminum Starch Octenylsuccinate, Aloe Barbadensis Leaf Extract, Witch Hazel Distillate,

Tocopheryl Acetate (Vitamin E), Charcoal Powder